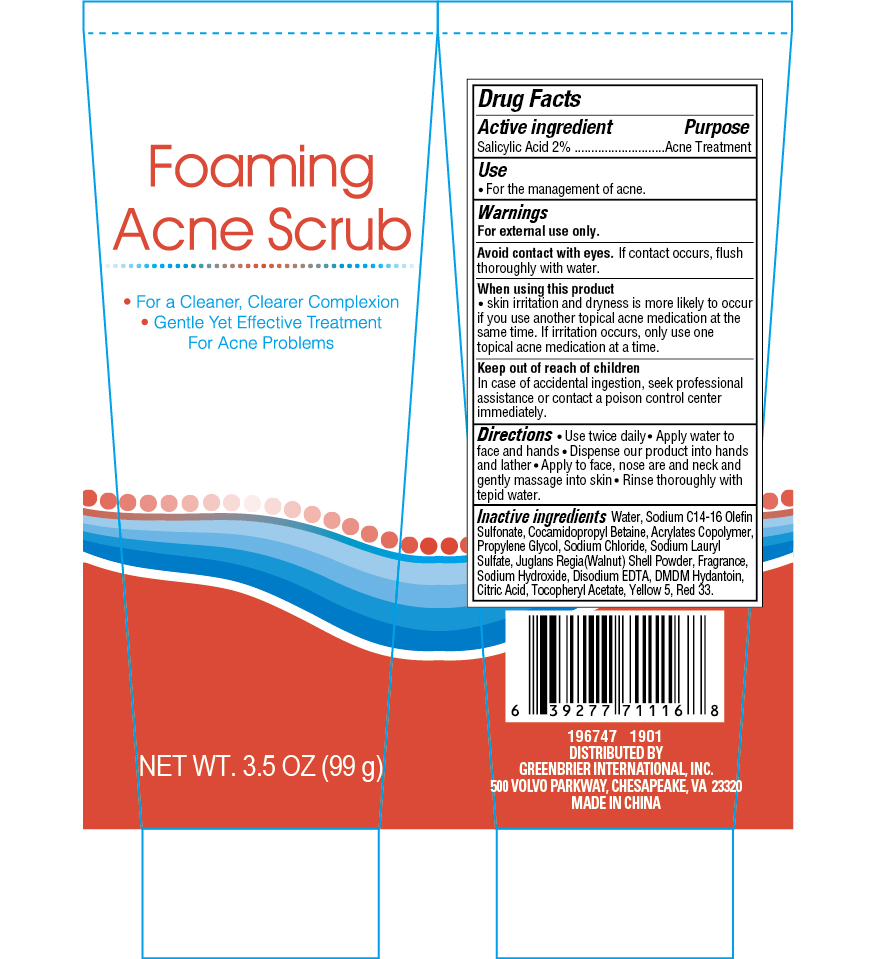 DRUG LABEL: Foaming acne scrub
NDC: 33992-3038 | Form: GEL
Manufacturer: Greenbrier International Inc.
Category: otc | Type: HUMAN OTC DRUG LABEL
Date: 20181218

ACTIVE INGREDIENTS: SALICYLIC ACID 2 g/100 g
INACTIVE INGREDIENTS: DMDM HYDANTOIN; FD&C YELLOW NO. 5; D&C RED NO. 33; BUTYL ACRYLATE/METHYL METHACRYLATE/METHACRYLIC ACID COPOLYMER (18000 MW); PROPYLENE GLYCOL; JUGLANS REGIA SHELL; SODIUM CHLORIDE; SODIUM C14-16 OLEFIN SULFONATE; SODIUM LAURYL SULFATE; .ALPHA.-TOCOPHEROL ACETATE, D-; WATER; COCAMIDOPROPYL BETAINE; CITRIC ACID MONOHYDRATE; ALOE VERA LEAF; DISODIUM EDTA-COPPER; SODIUM HYDROXIDE

Foaming Acne Scrub 3.5 oz

Purpose

Acne treatment

Active Ingredient

Salicylic Acid 2%

Directions

- Use twice daily
- Apply water to face and hands
- Dispense our product into hands and lather
- Apply to face, nose area and neck and gently massage into skin
- Rinse thoroughly with tepid water

Keep out of reach of children

If case of accidental ingestion, seek professional assistance or contact a poison control center immediately.

INACTIVE INGREDIENT

WATER, SODIUM C14-16 OLEFIN SULFONATE, COCAMIDOPROPYL BETAINE, ACRYLATES COPOLYMER, PROPYLENE GLYCOL, SODIUM CHLORIDE, SODIUM LAURYL SULFATE, JUGLANS REGIA (WALNUT) SHELL POWDER, FRAGRANCE, SODIUM HYDROXIDE, DISODIUM EDTA, DMDM HYDRONTOIN, CIRTIC ACID, TOCOPHERYL ACETATE, YELLOW 5, RED 33

Warnings

For external use only

When using this product

- Skin irritation and dryness are more likely to occur if you use another topical acne medication at the same time. If irritation occurs, oinly use one topical acne medication at a time.
- Avoid contact with eyes. If contact occurs, rinse thoroughly with water

Use

- For the management of acne